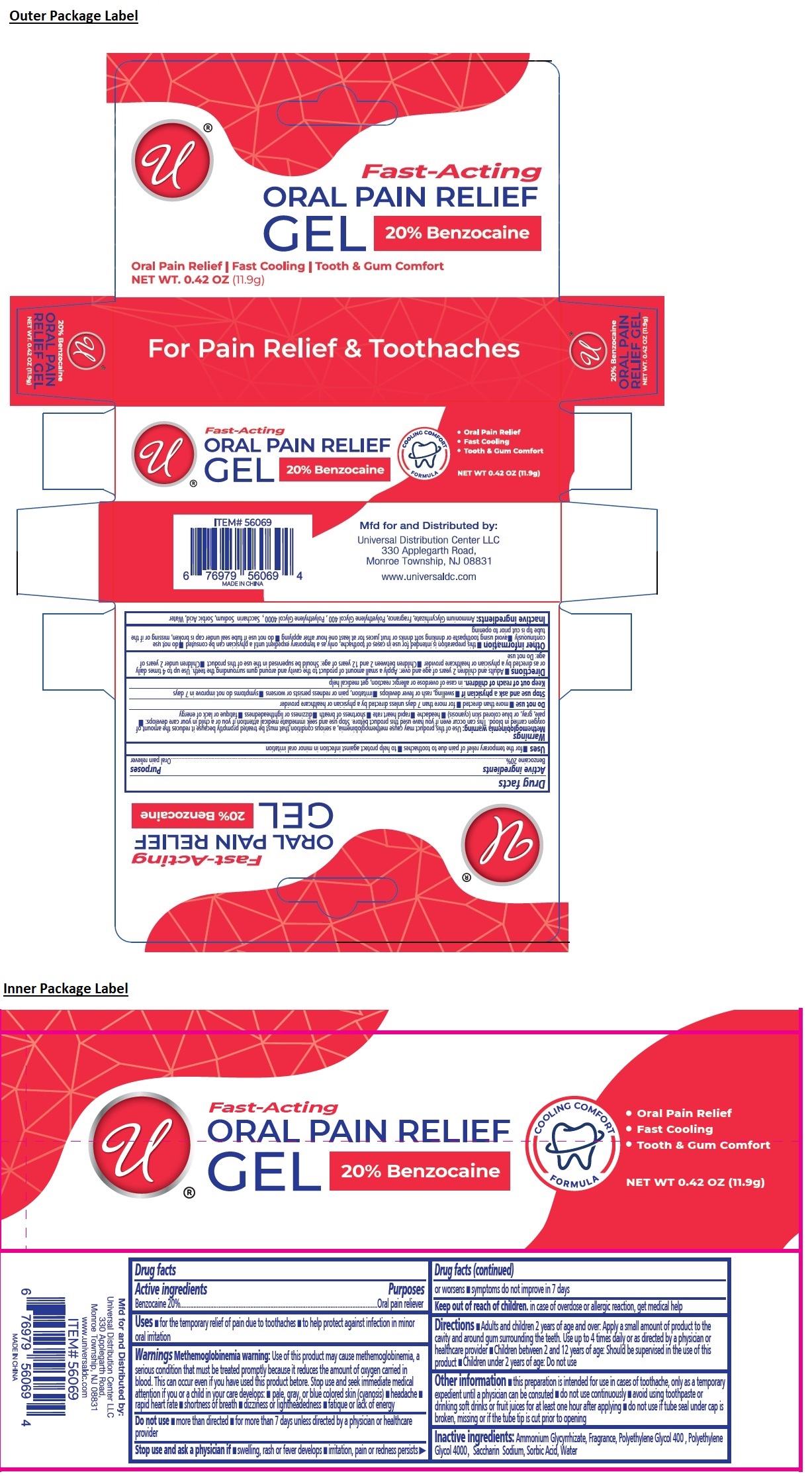 DRUG LABEL: ORAL PAIN RELIEF
NDC: 52000-443 | Form: GEL
Manufacturer: Universal Distribution Center LLC
Category: otc | Type: HUMAN OTC DRUG LABEL
Date: 20260120

ACTIVE INGREDIENTS: BENZOCAINE 20 g/100 g
INACTIVE INGREDIENTS: AMMONIUM GLYCYRRHIZATE; POLYETHYLENE GLYCOL 400; POLYETHYLENE GLYCOL 4000; SACCHARIN SODIUM; SORBIC ACID; WATER

Fast-Acting ORAL PAIN RELIEF GEL

Active ingredients

Benzocaine 20%

Purposes

Oral pain reliever

Uses

• for the temporary relief of pain due to toothaches • to help protect against infection in minor oral irritation

Warnings

Methemoglobinemia warning: Use of this product may cause methemoglobinemia, a serious condition that must be treated promptly because it reduces the amount of oxygen carried in blood. This can occur even if you have used this product before. Stop use and seek immediate medical attention if you or a child in your care develops: • pale, gray, or blue colored skin (cyanosis) • headache • rapid heart rate • shortness of breath • dizziness or lightheadedness • fatigue or lack of energy

Do not use • more than directed • for more than 7 days unless directed by a physician or healthcare provider

Stop use and ask a physician if • swelling, rash or fever develops • irritation, pain or redness persists or worsens • symptoms do not improve in 7 days

Keep out of reach of children. in case of overdose or allergic reaction, get medical help

Directions

• Adults and children 2 years of age and over: Apply a small amount of product to the cavity and around gum surrounding the teeth. Use up to 4 times daily or as directed by a physician or healthcare provider • Children between 2 and 12 years of age: Should be supervised in the use of this product • Children under 2 years of age: Do not use

Other information

• this preparation is intended for use in cases of toothache, only as a temporary expedient until a physician can be consulted • do not use continuosly • avoid using toothpaste or drinking soft drinks or fruit juices for at least one hour after applying • do not use if tube seal under cap is broken, missing or if the tube tip is cut prior to opening

Inactive ingredients

Ammonium Glycyrrhizate, Fragrance, Polyethylene Glycol 400, Polyethylene Glycol 4000, Saccharin Sodium, Sorbic Acid, Water

COOLING COMFORT FORMULA

• FAST COOLING
• TOOTH & GUM COMFORT

For Pain Relief & Toothaches

Mfd for and Distributed by:

Universal Distribution Center LLC
330 Applegarth Road,
Monroe Township, NJ 08831

www.universaldc.com

MADE IN CHINA